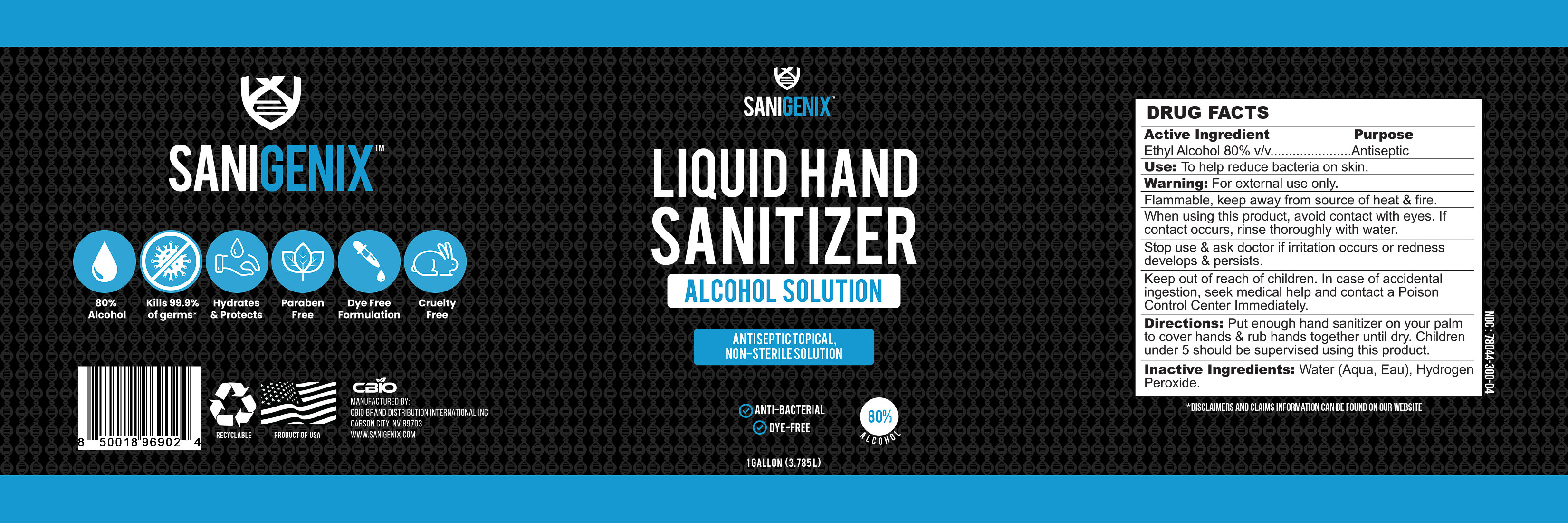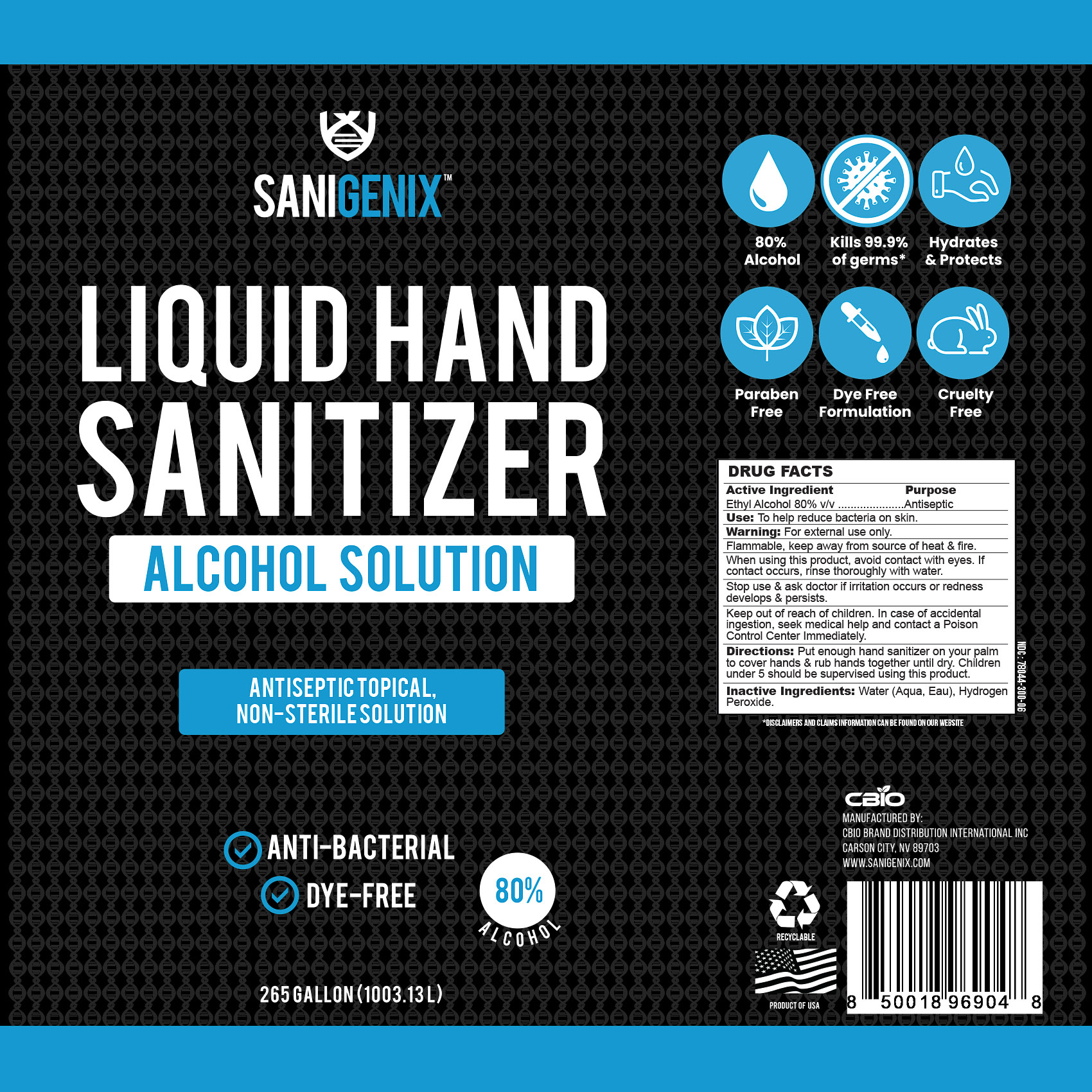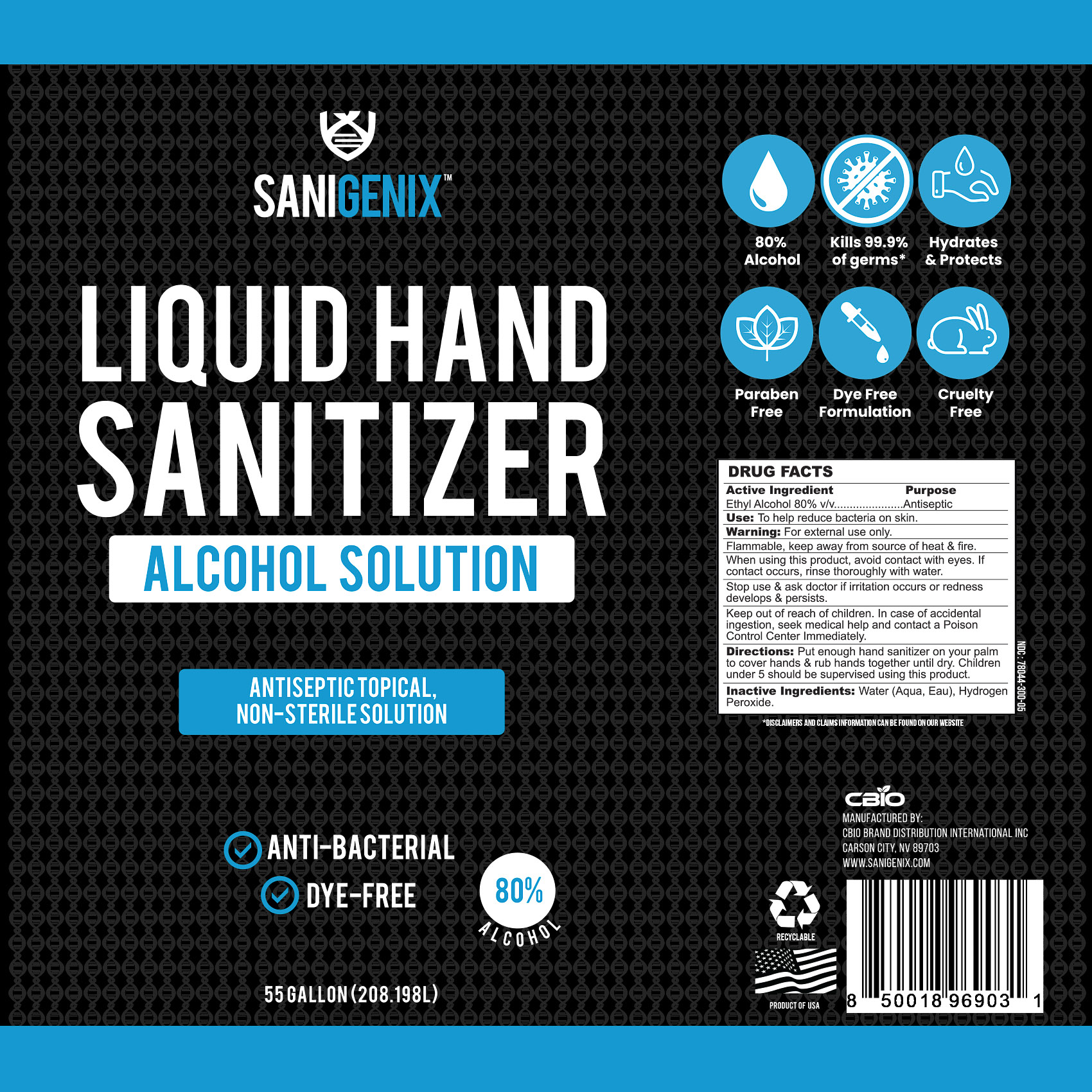 DRUG LABEL: Sanigenix Liquid Hand Sanitizer
NDC: 78044-300 | Form: LIQUID
Manufacturer: CBIO Brand Distribution  International Inc.
Category: otc | Type: HUMAN OTC DRUG LABEL
Date: 20200611

ACTIVE INGREDIENTS: ALCOHOL 80 mL/100 mL
INACTIVE INGREDIENTS: HYDROGEN PEROXIDE 0.125 mL/100 mL; WATER

80% Liquid Hand Sanitizer

This is a hand sanitizer manufactured according to the Temporary Policy for Preparation of Certain Alcohol-Based Hand Sanitizer Products During the Public Health Emergency (CoViD-19); Guidance for Industry.

The hand sanitizer is manufactured using only the following United States Pharmacopoeia (USP) grade ingredients in the preparation of the product (percentage in final product formulation) consistent with World Health Organization (WHO) recommendations:

1. Alcohol (ethanol) (USP or Food Chemical Codex (FCC) grade) (80%, volume/volume (v/v)) in an aqueous solution denatured according to Alcohol and Tobacco Tax and Trade Bureau regulations in 27 CFR part 20.
2. Hydrogen peroxide (0.125% v/v).
3. Sterile distilled water or boiled cold water.

The firm does not add other active or inactive ingredients. Different or additional ingredients may impact the quality and potency of the product.

Active Ingredient(s)

Ethyl Alcohol 80% v/v. Purpose: Antiseptic

Purpose

Antiseptic, Hand Sanitizer

Use

To help reduce bacteria on skin.

Warnings

For external use only. Flammable, keep away from source of heat & fire.

When using this product, avoid contact with eyes. If contact occurs, rinse thoroughly with water.

Stop use & ask doctor if irritation or rash occurs or redness develops & persists.

Keep out of reach of children. In case of accidental ingestion, seek medical help and contact a Poison Control Center Immediately.

Directions

Put enough hand sanitizer on your palm to cover hands & rub hands together until dry. Children under 5 should be supervised using this product.

Inactive ingredients

Water (Aqua, Eau), Hydrogen Peroxide

RECENT MAJOR CHANGES

Section 4:

To help reduce bacteria on skin.

Section 9:

Put enough hand sanitizer on your palm to cover hands & rub hands together until dry.

Children under 5 should be supervised using this product.

Package Label - Principal Display Panel

1 GALLON (3.785L) NDC: 78044-300-04

55 GALLON (208.198L) NDC: 78044-300-05

265 GALLON (1003.13L) NDC: 78044-300-06